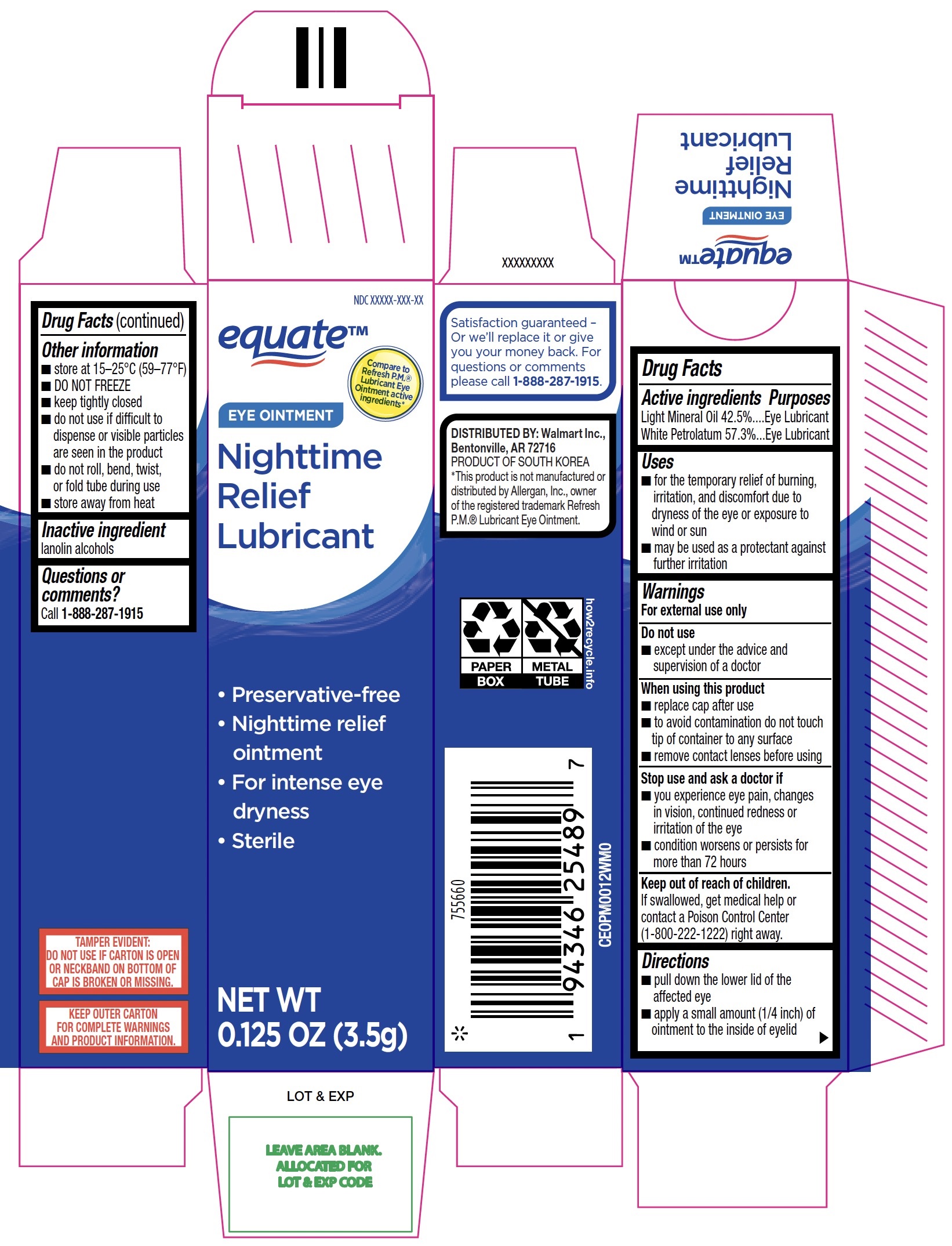 DRUG LABEL: Equate Nighttime Relief Lubricant
NDC: 79903-260 | Form: OINTMENT
Manufacturer: Walmart Inc.
Category: otc | Type: HUMAN OTC DRUG LABEL
Date: 20251230

ACTIVE INGREDIENTS: LIGHT MINERAL OIL 425 mg/1 g; WHITE PETROLATUM 573 mg/1 g
INACTIVE INGREDIENTS: LANOLIN ALCOHOLS

Equate Eye Ointment Nighttime Relief Lubricant 3.5g (PLD)

Active ingredients

Light Mineral Oil 42.5%

White Petrolatum 57.3%

Purposes

Eye Lubricant

Eye Lubricant

Uses

- for the temporary relief of burning, irritation, and discomfort due to dryness of the eye or exposure to wind or sun
- may be used as a protectant against further irritation

Warnings

For external use only

Do not use

- except under the advice and supervision of a doctor

When using this product

- replace cap after use
- to avoid contamination do not touch tip of container to any surface
- remove contact lenses before using

Stop use and ask a doctor if

- you experience eye pain, changes in vision, continued redness or irritation of the eye
- condition worsens or persists for more than 72 hours

Keep out of reach of children.

If swallowed, get medical help or contact a Poison Control Center (1-800-222-1222) right away.

Directions

- pull down the lower lid of the affected eye
- apply a small amount (1/4 inch) of ointment to the inside of eyelid

Inactive ingredient

lanolin alcohols

Questions or comments?

Call 1-888-287-1915